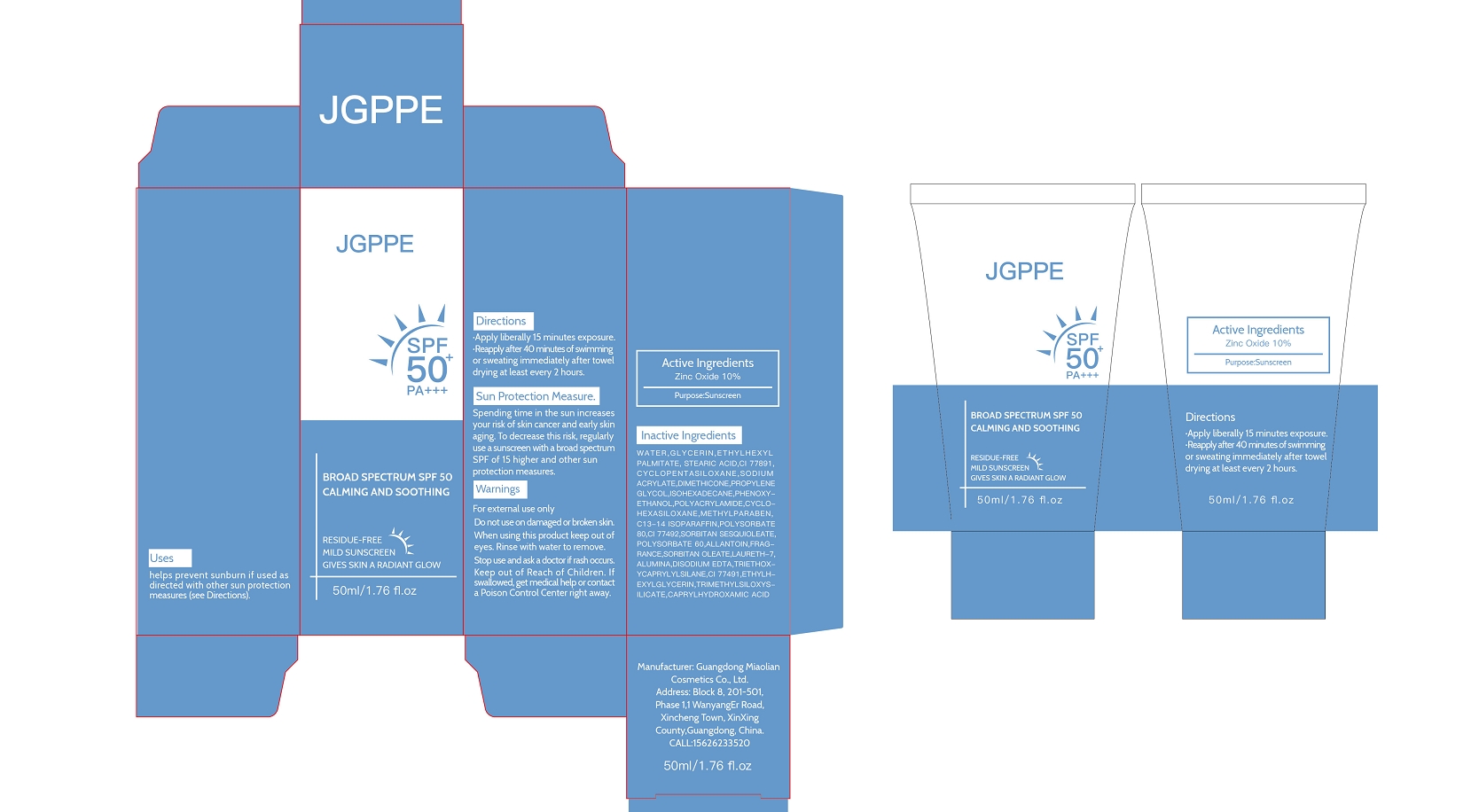 DRUG LABEL: JGPPE BROAD SPECTRUM SPF 50 SUNSCREEN
NDC: 84507-033 | Form: LOTION
Manufacturer: Guangdong Miaolian Cosmetics Co., Ltd.
Category: otc | Type: HUMAN OTC DRUG LABEL
Date: 20250304

ACTIVE INGREDIENTS: ZINC OXIDE 10 mg/100 mL
INACTIVE INGREDIENTS: DIMETHICONE; POLYACRYLAMIDE (1500 MW); CYCLOPENTASILOXANE; FRAGRANCE 13576; TRIMETHYLSILOXYSILICATE (M/Q 0.8-1.0); SORBITAN SESQUIOLEATE; POLYSORBATE 60; STEARIC ACID; METHYLPARABEN; CI 77891; PHENOXYETHANOL; WATER; ALLANTOIN; GLYCERIN; CI 77491; DIPROPYLENE GLYCOL; CI 77492; SODIUM ACRYLATE/SODIUM ACRYLOYLDIMETHYLTAURATE COPOLYMER (4000000 MW); TRIETHOXYCAPRYLYLSILANE; ISOHEXADECANE; ETHYLHEXYL PALMITATE; SORBITAN OLEATE; EDETATE DISODIUM; CYCLOHEXASILOXANE; LAURETH-7; ALUMINA; CAPRYLHYDROXAMIC ACID; ETHYLHEXYLGLYCERIN; C13-14 ISOPARAFFIN; POLYSORBATE 80

ACTIVE INGREDIENT

Zinc Oxide -----10%

PURPOSE

Helps prevent sunburn

If used as directed with other sun protection measures (see Directions), decreases the risk of skincancer and early skin aging caused by the sun

Keep out of reach of children

INDICATIONS AND USAGE

.Apply liberally 15 minutes exposure.

.Reapply after 40 minutes of swimmingor sweating immediately after toweldrying at least every 2 hours

WARNINGS

For external use only

Do not use on damaged or broken skin.

When using this product keep out of eyes. Rinse with water to remove.Stop use and ask a doctor if rash occurs.

Keep out of Reach of Children. lf swallowed, get medical help or contacta Poison Control Center right away.

DOSAGE AND ADMINISTRATION

Sun Protection Measures Spending time in the sun increases your risk of skin cancer and early skin aging. To decrease this risk, regularly use a sunscreen with a Broad Spectrum SPF value of 15 or higher and other sub and other sun protection measures including:
Limit time in the sun, especially from 10 a.m.- 2 p.m.
Wear long-sleeved shirts, pants, hats and sunglasses
Children under 6 months: Ask a doctor

INACTIVE INGREDIENT

WATER,GLYCERIN,ETHYLHEXYL PALMITATE,STEARIC ACID,CI 77891,CYCLOPENTASILOXANE,SODIUM ACRYLATE/SODIUM ACRYLOYLDIMETHYL TAURATE COPOLYMER,DIMETHICONE,PROPYLENE GLYCOL,ISOHEXADECANE,PHENOXYETHANOL,POLYACRYLAMIDE,CYCLOHEXASILOXANE,METHYLPARABEN,C13-14 ISOPARAFFIN,POLYSORBATE 80,CI 77492,SORBITAN SESQUIOLEATE,POLYSORBATE 60,ALLANTOIN,FRAGRANCE,SORBITAN OLEATE,LAURETH-7,ALUMINA,DISODIUM EDTA,TRIETHOXYCAPRYLYLSILANE,CI 77491,ETHYLHEXYLGLYCERIN,TRIMETHYLSILOXYSILICATE,CAPRYLHYDROXAMIC ACID